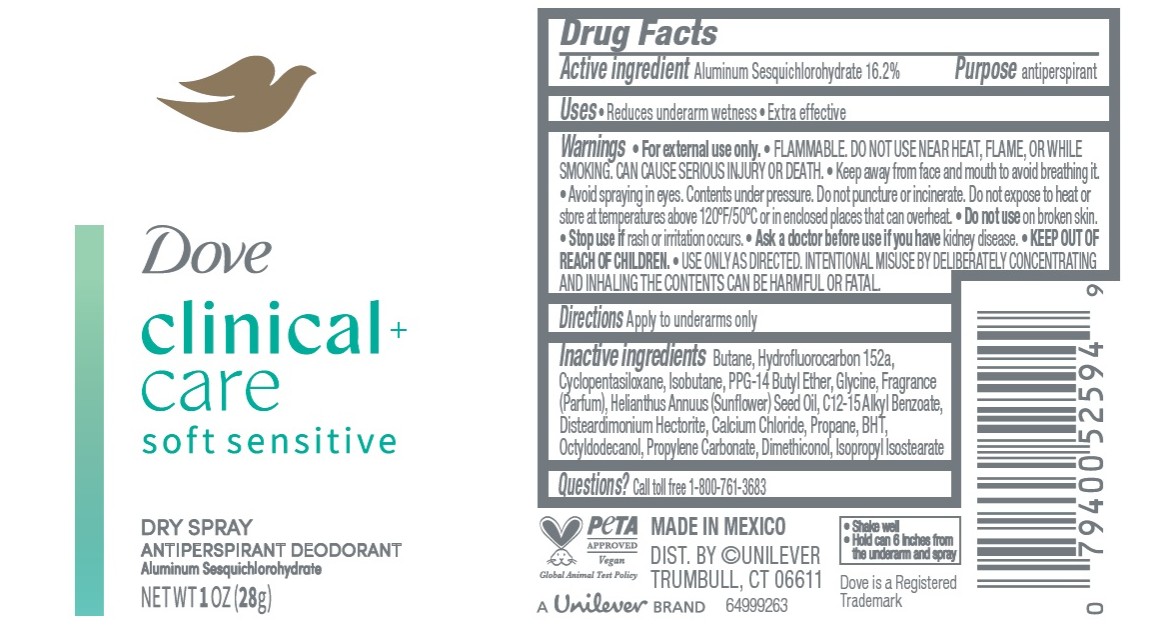 DRUG LABEL: Dove Clinical Care
NDC: 64942-2420 | Form: AEROSOL, SPRAY
Manufacturer: Conopco d/b/a Unilever
Category: otc | Type: HUMAN OTC DRUG LABEL
Date: 20251219

ACTIVE INGREDIENTS: ALUMINUM SESQUICHLOROHYDRATE 16.2 g/100 g
INACTIVE INGREDIENTS: GLYCINE; BUTANE; HYDROFLUOROCARBON 152A; CYCLOPENTASILOXANE; C12-15 ALKYL BENZOATE; DISTEARDIMONIUM HECTORITE; OCTYLDODECANOL; PROPYLENE CARBONATE; ISOBUTANE; ISOPROPYL ISOSTEARATE; PPG-14 BUTYL ETHER; HELIANTHUS ANNUUS (SUNFLOWER) SEED OIL; PROPANE; BHT; DIMETHICONOL (2000 CST); CALCIUM CHLORIDE

Dove Clinical + Care Soft Sensitive Dry Spray Antiperspirant Deodorant

DESCRIPTION

Dove Clinical + Care Soft Sensitive Dry Spray Antiperspirant Deodorant

ACTIVE INGREDIENT

Aluminum Sesquichlorohydrate 16.2%

PURPOSE

Antiperspirant

INDICATIONS AND USAGE

• Reduces underarm wetness

• Extra effective

WARNINGS

• For external use only.
• FLAMMABLE. DO NOT USE NEAR HEAT, FLAME, OR WHILE SMOKING. CAN CAUSE SERIOUS INJURY OR DEATH.
• Keep away from face and mouth to avoid breathing it.
• Avoid spraying in eyes. Contents under pressure. Do not puncture or incinerate. Do not expose to heat or store at temperatures above 120°F/50°C or in enclosed places that can overheat.
• Do not use on broken skin. • Stop use if rash or irritation occurs.• Ask a doctor before use if you have kidney disease. • USE ONLY AS DIRECTED. INTENTIONAL MISUSE BY DELIBERATELY CONCENTRATING AND INHALING THE CONTENTS CAN BE HARMFUL OR FATAL.

• KEEP OUT OF REACH OF CHILDREN.

DOSAGE AND ADMINISTRATION

apply to underarms only

INACTIVE INGREDIENT

Butane, Hydrofluorocarbon 152a,
Cyclopentasiloxane, Isobutane, PPG-14 Butyl Ether, Glycine, Fragrance
(Parfum), Helianthus Annuus (Sunflower) Seed Oil, C12-15 Alkyl Benzoate,
Disteardimonium Hectorite, Calcium Chloride, Propane, BHT,
Octyldodecanol, Propylene Carbonate, Dimethiconol, Isopropyl Isostearate

QUESTIONS

Call 1-800-761-3683